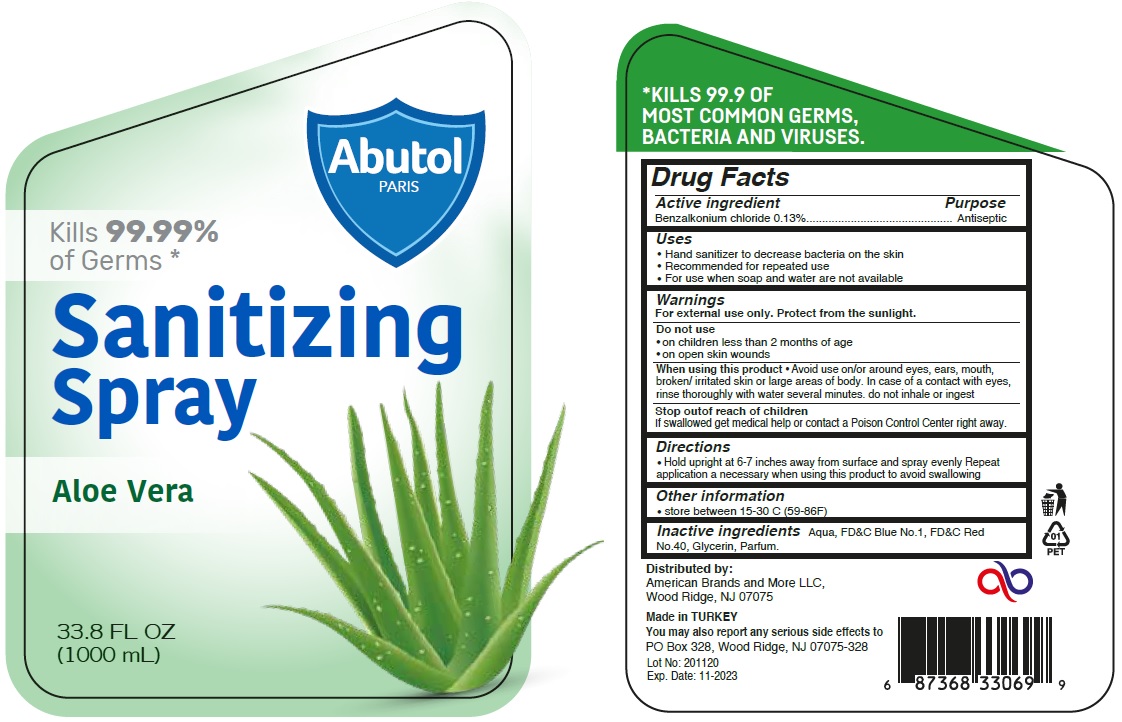 DRUG LABEL: Abutol Sanitizing Aloe Vera
NDC: 77418-803 | Form: SPRAY
Manufacturer: ATAK FARMA KOZMETIK VE KIMYA SANAYI TICARET ANONIM SIRKETI
Category: otc | Type: HUMAN OTC DRUG LABEL
Date: 20201105

ACTIVE INGREDIENTS: BENZALKONIUM CHLORIDE 0.13 g/100 mL
INACTIVE INGREDIENTS: WATER; FD&C BLUE NO. 1; FD&C RED NO. 40; GLYCERIN

Abutol PARIS Sanitizing Spray Aloe Vera

Active ingredient

Benzalkonium chloride 0.13%

Purpose

Antiseptic

Uses

• Hand sanitizer to decrease bacteria on the skin
• Recommended for repeated use
• For use when soap and water are not available

Warnings

For external use only. Protect from the sunlight.

Do not use
• on children less than 2 months of age
• on open skin wounds

When using this product • Avoid use on/or around eyes, ears, mouth, broken/ irritated skin or large areas of body. In case of a contact with eyes, rinse thoroughly with water several minutes. do not inhale or ingest

Stop out of reach of children
If swallowed get medical help or contact a Poison Control Center right away.

Directions

• Hold upright at 6-7 inches away from surface and spray evenly. Repeat application a necessary when using this product to avoid swallowing

Other information

• store between 15-30 C (59-86F)

Inactive ingredients

Aqua, FD&C Blue No.1, FD&C Red No.40, Glycerin, Parfum.

Kills 99.99% of Germs *

* KILLS 99.9 OF MOST COMMON GERMS, BACTERIA AND VIRUSES.

Distributed by:
American Brands and More LLC,
Wood Ridge, NJ 07075

Made in TURKEY
You may also report any serious side effects to
PO Box 328, Wood Ridge, NJ 07075-328